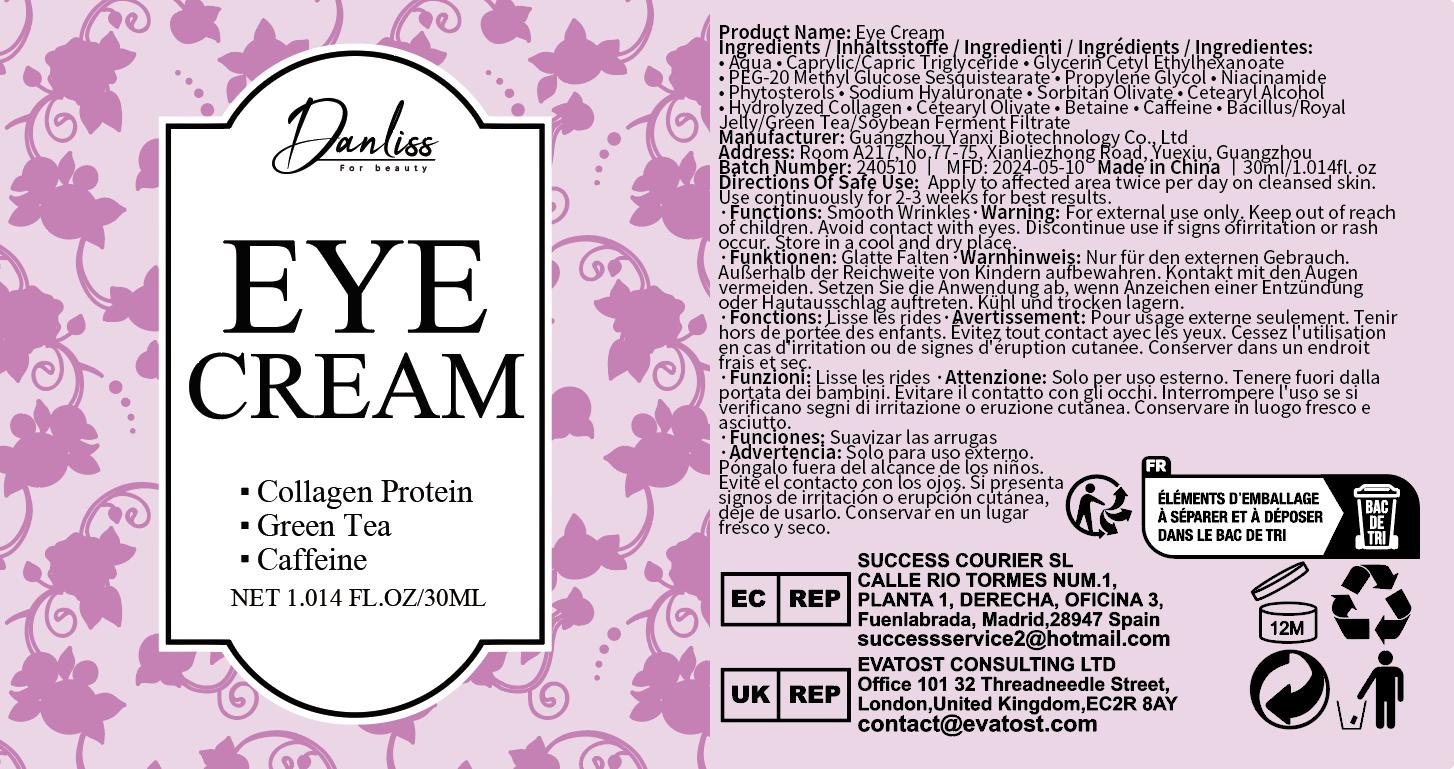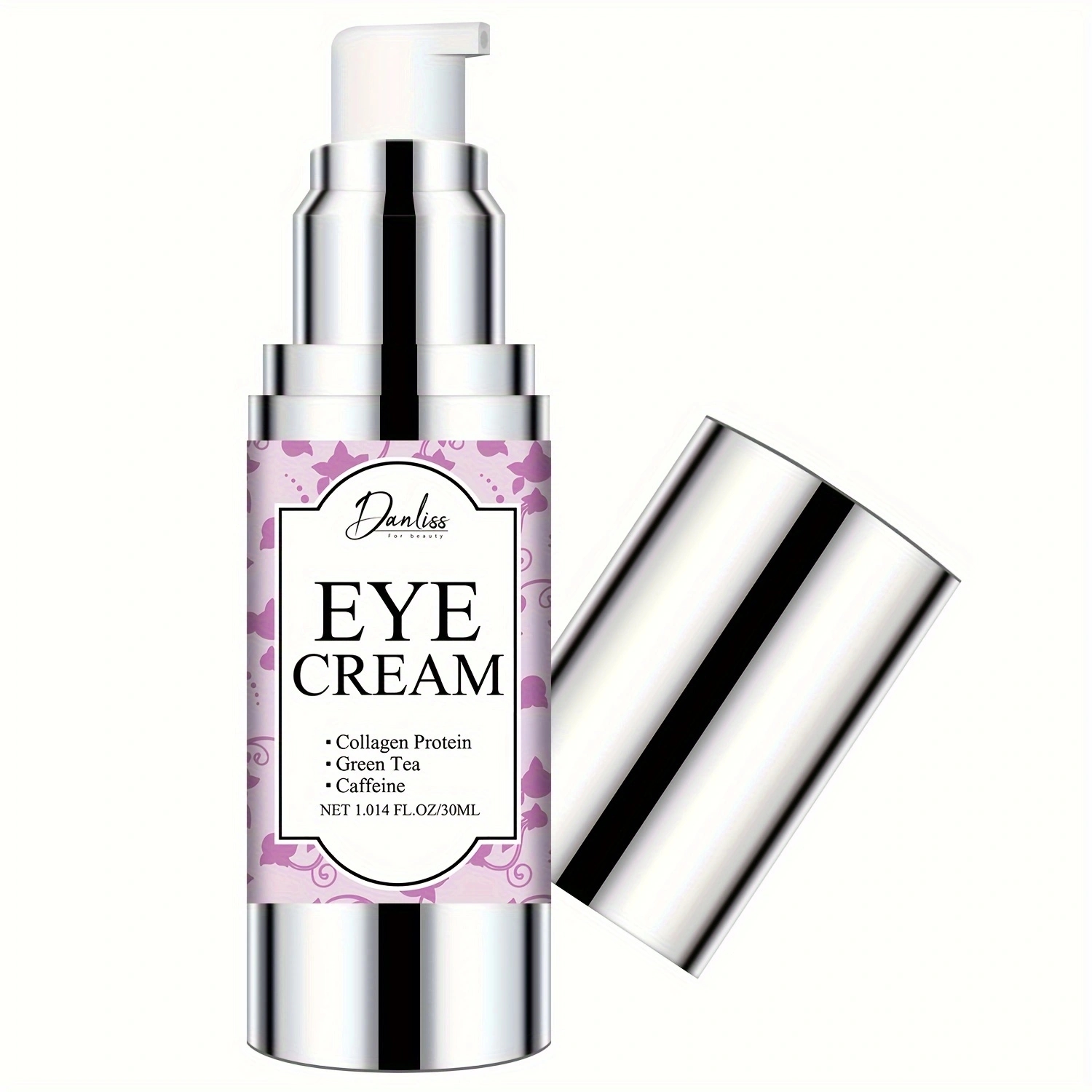 DRUG LABEL: Eye Cream
NDC: 84025-245 | Form: CREAM
Manufacturer: Guangzhou Yanxi Biotechnology Co., Ltd
Category: otc | Type: HUMAN OTC DRUG LABEL
Date: 20241104

ACTIVE INGREDIENTS: CAPRYLIC/CAPRIC TRIGLYCERIDE 5 mg/100 mL; PEG-20 METHYL GLUCOSE SESQUISTEARATE 3 mg/100 mL
INACTIVE INGREDIENTS: WATER

DOSAGE AND ADMINISTRATION

Apply to affected area twice per day on cleansed skin. Use continuously for 2-3 weeks for best results.

WARNINGS

keep out of children

INACTIVE INGREDIENT

Aqua

INDICATIONS AND USAGE

for daily eyes care

kepp out of children

PURPOSE

Smooth Wrinkles